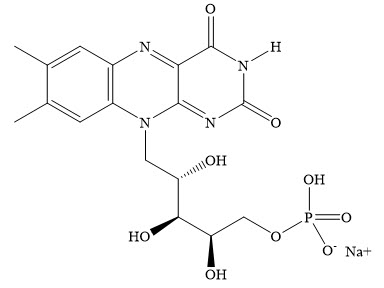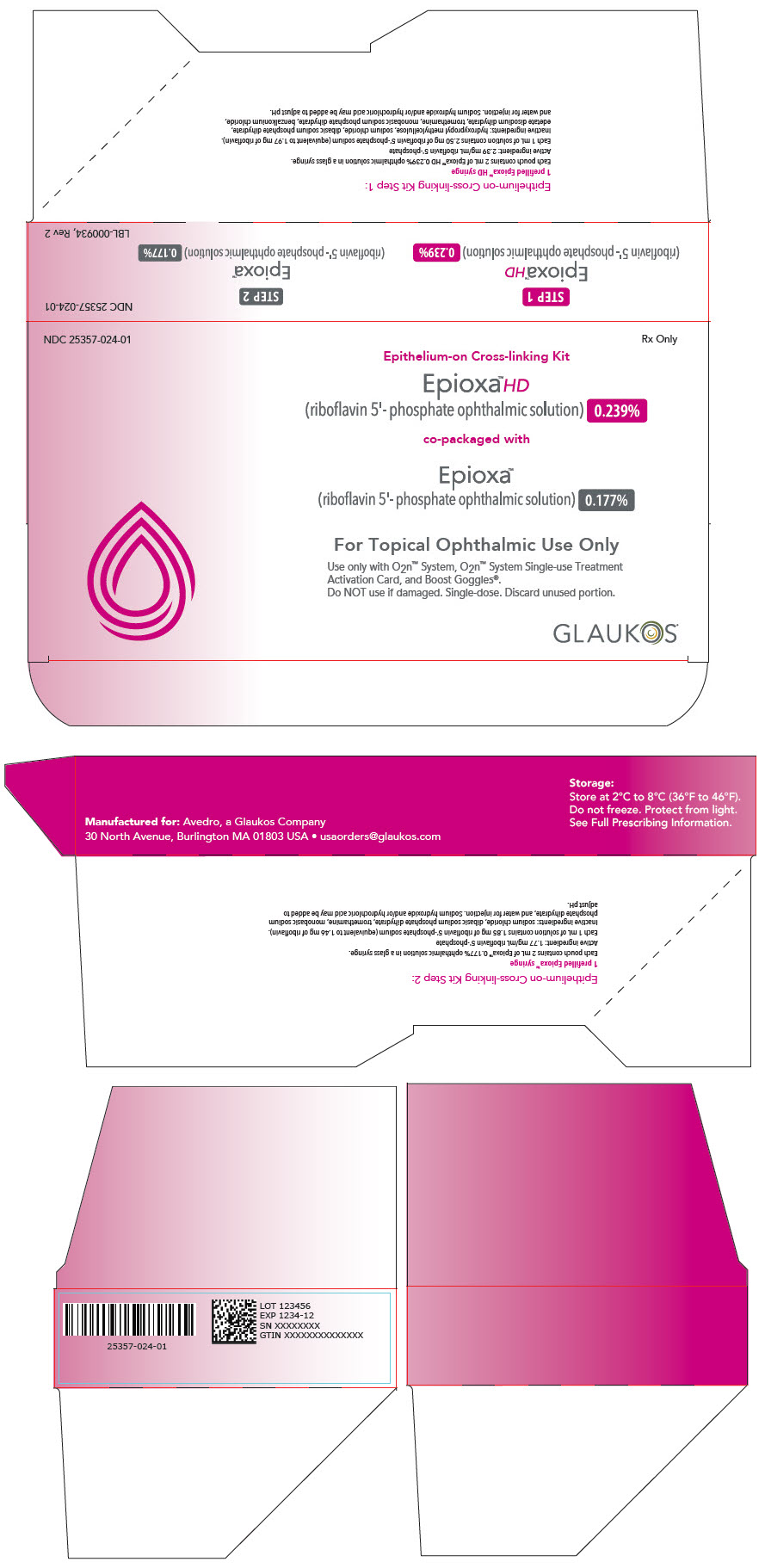 DRUG LABEL: EPIOXA CROSS-LINKING
NDC: 25357-024 | Form: KIT | Route: OPHTHALMIC
Manufacturer: Glaukos Corporation
Category: prescription | Type: HUMAN PRESCRIPTION DRUG LABEL
Date: 20251118

ACTIVE INGREDIENTS: RIBOFLAVIN 5'-PHOSPHATE 2.39 mg/1 mL; RIBOFLAVIN 5'-PHOSPHATE 1.77 mg/1 mL

HIGHLIGHTS OF PRESCRIBING INFORMATION

These highlights do not include all the information needed to use EPIOXA™ HD and EPIOXA™ safely and effectively. See full prescribing information for EPIOXA HD and EPIOXA.
EPIOXA HD (riboflavin 5'-phosphate ophthalmic solution) 0.239%, for topical ophthalmic use
EPIOXA (riboflavin 5'-phosphate ophthalmic solution) 0.177%, for topical ophthalmic use
For use with the O2n™ System and Boost Goggles®
Initial U.S. Approval: 2016

1 INDICATIONS AND USAGE

EPIOXA HD and EPIOXA are photoenhancers indicated for use in epithelium-on corneal collagen cross-linking for the treatment of keratoconus in adults and pediatric patients aged 13 years and older, in conjunction with the O2n System and the Boost Goggles (1).

2 DOSAGE AND ADMINISTRATION

- Apply topical anesthetic and insert a lid speculum (2).
- Using a cellulose spear sponge soaked with EPIOXA HD, remove the mucin layer from the corneal surface without debriding the corneal epithelium (epithelium-on) by swiping the sponge 4 to 10 times horizontally and vertically (2).
- Apply two drops of EPIOXA HD topically on the eye every 60 seconds for 4 minutes (STEP 1), followed by two drops of EPIOXA topically on the eye every 30 seconds for 6 minutes (STEP 2) (2).
- Gently rinse the corneal surface with approximately 5 mL of balanced salt solution (BSS) (2).
- Perform ultrasound pachymetry. If corneal thickness is less than 325 microns, irradiation should not be performed (2).
- Apply the Boost Goggles and turn on the oxygen flow. Refer to the Boost Goggles User Guide (2).
- Center the optical head of the O2n System over the cornea and irradiate the eye as per the instructions in the O2n System Operator's Manual. The O2n System automatically delivers irradiation to the eye for 11 minutes 6 seconds at 30 mW/cm^2 with an on/off cycle of 1 second UV-A on/ 1 second UV-A off at a wavelength of 365 nm (2).
- Instill BSS on the cornea every 2 minutes, or more frequently as needed, to maintain corneal hydration during UV-A irradiation (2).
- When the UV-A irradiation has stopped, shut off the oxygen flow and remove the Boost Goggles and lid speculum (2).
- Apply a bandage contact lens (2).

3 DOSAGE FORMS AND STRENGTHS

- Ophthalmic solution: EPIOXA HD 0.239% in a single-dose glass syringe (3.1)
- Ophthalmic solution: EPIOXA 0.177% in a single-dose glass syringe (3.2)

4 CONTRAINDICATIONS

- Hypersensitivity (4.1)
- Aphakic and pseudophakic patients without a UV-blocking intraocular lens (4.2)

5 WARNINGS AND PRECAUTIONS

Herpetic keratitis: Use with caution in patients with a history of herpetic keratitis due to the potential for reactivation (5).

6 ADVERSE REACTIONS

The most common adverse reaction was conjunctival hyperaemia (31%). Other adverse reactions, occurring in 5% to 25% of eyes included: corneal opacity (haze), photophobia, punctate keratitis, eye pain, eye irritation, increased lacrimation, corneal epithelium defect, eyelid oedema, corneal striae, visual acuity reduced, dry eye, and anterior chamber flare (6.1).

To report SUSPECTED ADVERSE REACTIONS, contact GLAUKOS CORPORATION at 1-888-404-1644 or FDA at 1-800-FDA-1088 or www.fda.gov/medwatch.

FULL PRESCRIBING INFORMATION

1 INDICATIONS AND USAGE

EPIOXA HD and EPIOXA are indicated in epithelium-on corneal collagen cross-linking for the treatment of keratoconus in adults and pediatric patients aged 13 years and older, in conjunction with the O2n System and the Boost Goggles.

2 DOSAGE AND ADMINISTRATION

2.1 Important Administration Instructions

EPIOXA HD and EPIOXA are for topical ophthalmic use. NOT for injection or intraocular use.

EPIOXA HD and EPIOXA are supplied in single-dose syringes. Discard opened syringes after use.

EPIOXA HD and EPIOXA are for use with the O2n System and Boost Goggles only.

Refer to the O2n System Operator's Manual and Boost Goggles User Guide for device instructions.

2.2 Recommended Dosage and Administration Instructions

Apply topical anesthetic and insert a lid speculum.

Using a cellulose spear sponge soaked with EPIOXA HD, remove the mucin layer from the corneal surface without debriding the corneal epithelium (epithelium-on) by swiping the sponge 4 to 10 times horizontally and vertically.

Apply two drops of EPIOXA HD topically on the eye every 60 seconds for 4 minutes (STEP 1), followed by two drops of EPIOXA topically on the eye every 30 seconds for 6 minutes (STEP 2).

Gently rinse the corneal surface with approximately 5 mL of balanced salt solution (BSS).

Perform ultrasound pachymetry. If corneal thickness is less than 325 microns, irradiation should not be performed.

Apply the Boost Goggles and turn on the oxygen flow as per the instructions in the Boost Goggles User Guide.

Center the optical head of the O2n System over the cornea and irradiate the eye as per the instructions in the O2n System Operator's Manual. The O2n System automatically delivers irradiation to the eye for 11 minutes 6 seconds at 30 mW/cm^2 with an on/off cycle of 1 second UV-A on/1 second UV-A off at a wavelength of 365 nm.

Instill BSS on the cornea every 2 minutes, or more frequently as needed, to maintain corneal hydration during UV-A irradiation.

When the UV-A irradiation has stopped, shut off the oxygen flow, and remove the Boost Goggles and lid speculum.

Apply a bandage contact lens.

3 DOSAGE FORMS AND STRENGTHS

3.1 EPIOXA HD

Ophthalmic solution: 0.239% (2.39 mg/mL) of riboflavin 5'-phosphate in a clear, yellow, solution in a single-dose glass syringe.

3.2 EPIOXA

Ophthalmic solution: 0.177% (1.77 mg/mL) of riboflavin 5'-phosphate in a clear, yellow, solution in a single-dose glass syringe.

4 CONTRAINDICATIONS

4.1 Hypersensitivity

EPIOXA HD and EPIOXA are contraindicated in patients with known hypersensitivity to benzalkonium chloride or any ingredients in EPIOXA HD and EPIOXA.

4.2 Aphakic and Pseudophakic Patients

Epithelium-on corneal collagen cross-linking is contraindicated in aphakic patients and pseudophakic patients without a UV-blocking intraocular lens.

5 WARNINGS AND PRECAUTIONS

5.1 Herpetic Keratitis

Corneal collagen cross-linking should be used with caution in patients with a history of herpetic keratitis due to the potential for reactivation of herpes keratitis.

6 ADVERSE REACTIONS

The following clinically significant adverse reactions are described elsewhere in the labeling:

Herpetic keratitis [see Warnings and Precautions (5.1)]

6.1 Clinical Trials Experience

Because clinical trials are conducted under widely varying conditions, adverse reaction rates observed in the clinical trials of a drug cannot be directly compared to rates in the clinical trials of another drug and may not reflect the rates observed in practice.

The safety of EPIOXA HD and EPIOXA in the epithelium-on corneal collagen cross-linking procedure with UV-A irradiation and supplemental oxygen was evaluated in two randomized, parallel-group, sham procedure/vehicle-controlled trials. Study eyes were randomized in a 2:1 treatment allocation to receive corneal collagen cross-linking (CXL) or sham procedure/vehicle control at the baseline visit. In both trials, CXL-treated eyes were followed for 12 months.

Safety data were obtained from a total of 389 CXL-treated eyes.

The most commonly reported adverse reaction in CXL-treated eyes was conjunctival hyperaemia (31%). Other adverse reactions occurring in 5% to 25% of CXL-treated eyes included: corneal opacity (haze), photophobia, punctate keratitis, eye pain, eye irritation, lacrimation increased, corneal epithelium defect, eyelid oedema, corneal striae, visual acuity reduced, dry eye, and anterior chamber flare.

8 USE IN SPECIFIC POPULATIONS

8.1 Pregnancy

Risk Summary

Animal development and reproduction studies have not been conducted with EPIOXA HD and EPIOXA with the O2n System and Boost Goggles. Since it is not known whether the epithelium-on corneal collagen cross-linking procedure can cause fetal harm or affect reproduction capacity, it should not be performed on pregnant women.

8.2 Lactation

Risk Summary

There are no data on the presence of EPIOXA HD or EPIOXA in human milk, the effects on the breastfed infant, or the effects on milk production. The developmental and health benefits of breastfeeding should be considered, along with the mother's clinical need for the EPIOXA HD and EPIOXA epithelium-on corneal collagen cross-linking procedure and any potential adverse effects on the breastfed child from the EPIOXA HD and EPIOXA epithelium-on corneal collagen cross-linking procedure or from the underlying maternal condition.

8.4 Pediatric Use

The safety and effectiveness of EPIOXA HD and EPIOXA for the treatment of keratoconus have been established in pediatric patients aged 13 years and older.

8.5 Geriatric Use

No patients enrolled in the clinical trials were 65 years of age or older.

11 DESCRIPTION

EPIOXA HD (riboflavin 5'-phosphate ophthalmic solution) 0.239% and EPIOXA (riboflavin 5'-phosphate ophthalmic solution) 0.177% contain riboflavin 5'-phosphate, a photoenhancer, for topical ophthalmic use.

EPIOXA HD 0.239% is a clear, yellow, sterile buffered solution containing 2.39 mg/mL riboflavin 5'-phosphate. The pH of the solution is 6.7 to 7.7 and the osmolality is 200 mOsm/kg to 260 mOsm/kg. Each mL of solution contains 2.50 mg of riboflavin 5'-phosphate sodium (equivalent to 1.97 mg/mL riboflavin). Riboflavin 5'-phosphate sodium is a mixture of the sodium salts of riboflavin, riboflavin monophosphates, and riboflavin diphosphates. The inactive ingredients are hydroxypropyl methylcellulose, sodium chloride, dibasic sodium phosphate dihydrate, edetate disodium dihydrate, tromethamine, monobasic sodium phosphate dihydrate, benzalkonium chloride, and water for injection. Sodium hydroxide and/or hydrochloric acid may be added to adjust pH.

EPIOXA 0.177% is a clear, yellow, sterile buffered solution containing 1.77 mg/mL riboflavin 5'-phosphate. The pH of the solution is 6.5 to 7.5 and the osmolality is 330 mOsm/kg to 400 mOsm/kg. Each mL of solution contains 1.85 mg of riboflavin 5'-phosphate sodium (equivalent to 1.46 mg/mL riboflavin). Riboflavin 5'-phosphate sodium is a mixture of the sodium salts of riboflavin, riboflavin monophosphates, and riboflavin diphosphates. The inactive ingredients are sodium chloride, dibasic sodium phosphate dihydrate, tromethamine, monobasic sodium phosphate dihydrate, and water for injection. Sodium hydroxide and/or hydrochloric acid may be added to adjust pH.

The molecular formula for riboflavin 5'-phosphate sodium (Vitamin B2) is C17H20N4NaO9P with a molecular weight of 478.33 g/mol.

12 CLINICAL PHARMACOLOGY

12.1 Mechanism of Action

Riboflavin 5'-phosphate sodium (Vitamin B2) is the precursor of two coenzymes, flavin adenine dinucleotide and flavin mononucleotide, which catalyze oxidation/reduction reactions involved in a number of metabolic pathways.

Under the conditions used for corneal collagen cross-linking, riboflavin 5'-phosphate functions as a photoenhancer and generates singlet oxygen which is responsible for the cross-linking.

12.2 Pharmacodynamics

The pharmacodynamics of EPIOXA HD and EPIOXA have not been characterized.

12.3 Pharmacokinetics

The pharmacokinetics of EPIOXA HD and EPIOXA have not been characterized.

13 NONCLINICAL TOXICOLOGY

13.1 Carcinogenesis, Mutagenesis, Impairment of Fertility

Carcinogenicity

Animal studies have not been conducted to determine the carcinogenic potential of photoexcited riboflavin.

Mutagenesis

Photoexcited riboflavin has been shown to be genotoxic in the Ames Salmonella reverse mutation assay and in the SOS/umu test system.

The genotoxicity of riboflavin, in the absence of photoexcitation has been examined in vitro in bacterial reverse mutation assays, sister chromatid exchange assay, chromosomal aberration assays and in vivo in a mouse micronucleus study. The overall weight of evidence indicates that riboflavin, in the absence of photoexcitation, is not genotoxic.

Impairment of Fertility

Animal studies to determine the effects of the EPIOXA HD and EPIOXA epithelium-on corneal collagen cross-linking procedure on fertility were not conducted.

14 CLINICAL STUDIES

Two prospective, randomized, parallel-group, sham procedure/vehicle-controlled trials (Study 1 [NCT03442751] and Study 2 [NCT05759559]) were conducted to evaluate the safety and efficacy of epithelium-on corneal collagen cross-linking (CXL) using riboflavin 5'-phosphate ophthalmic solutions with UV-A irradiation and supplemental oxygen in patients with keratoconus.

In both trials, eligible eyes were randomized to receive CXL treatment or sham procedure/vehicle control in a 2:1 treatment allocation at the baseline visit. Aphakic patients and pseudophakic patients without a UV-blocking intraocular lens were excluded. Both eyes of a patient could be enrolled in the trial; however, one eye was treated first, and the second eye was treated between 1 week and 3 months after the first eye. Eyes were evaluated at 1 day, 3 days, 1 week, and 1, 3, 6, and 12 months post-treatment.

In Study 1, eyes randomized to sham procedure/vehicle control were permitted to receive CXL treatment after month 6 and were followed an additional 6 months. The primary efficacy endpoint was at month 6 post-treatment and the secondary efficacy endpoint was at month 12 post-treatment. In Study 2, the primary efficacy endpoint was at month 12 post-treatment and the secondary efficacy endpoint was at month 6 post-treatment.

In Study 1, a total of 280 eyes of 201 patients were randomized into the trial, of which 279 eyes were treated: 189 eyes received CXL treatment and 90 eyes initially received sham procedure/vehicle control. A statistically significant treatment effect was demonstrated at month 6, based on the difference in change from baseline in maximum corneal curvature (Kmax) between the CXL treatment group and sham procedure/vehicle control group (Table 1).

Table 1. Study 1: Mean Baseline Kmax (D) and Change from Baseline Kmax (D)
Visit | CXL Treatment (N=189) | Sham Procedure/ Vehicle Control (N=90) | Treatment Difference (95% CI) P-value
Baseline [Mean (standard deviation) Kmax] | 59.4 (9.1) | 59.3 (9.1)
Month 6 [LS Mean change from baseline and corresponding 95% CIs obtained from a RMMM ANCOVA model with treatment as a factor and the baseline Kmax value and baseline keratoconus severity as covariates. Missing post-baseline Kmax data were handled by multiple imputation procedure for month 6.] | -0.3 (-0.6, -0.0) | 0.6 (0.2, 1.1) | -1.0 (-1.5, -0.4) P<0.01
Month 12 [Missing post-baseline Kmax data were handled by last observation carried forward method for month 12 in Sham Procedure/Vehicle Control eyes that received CXL treatment after month 6.] | -0.4 (-0.7, -0.2) | 0.7 (0.3, 1.1) | -1.1 (-1.6, -0.6) P<0.01
Randomized eyes that received study treatment

In a subgroup analysis of patients in this trial at month 6, younger patients (< 29 years) experienced a treatment effect of -2.0 D, as a combination of improvement in the CXL treatment arm (-0.7 D) and deterioration in the sham procedure/vehicle control arm (1.3 D). Older patients (≥ 29 years) did not experience improvement at month 6 in either arm.

In Study 2, a total of 312 eyes of 208 patients were randomized into the trial, of which 312 eyes were treated: 200 eyes received CXL treatment and 112 eyes received sham procedure/vehicle control. A statistically significant treatment effect was demonstrated at month 12, based on the difference in change from baseline in Kmax between the CXL treatment group and sham procedure/vehicle control group (Table 2).

Table 2. Study 2: Mean Baseline Kmax (D) and Change from Baseline Kmax (D)
Visit | CXL Treatment (N=200) | Sham Procedure/ Vehicle Control (N=112) | Treatment Difference (95% CI) P-Value
Baseline [Mean (standard deviation) Kmax] | 58.0 (8.0) | 58.1 (8.6)
Month 6 [LS Mean change from baseline and corresponding 95% CIs obtained from a RMMM ANCOVA model with treatment as a factor and the baseline Kmax value and baseline keratoconus severity and age stratum as covariates. Missing post-baseline Kmax data were handled by multiple imputation procedure.] | -0.4 (-0.6, -0.2) | 0.1 (-0.1, 0.4) | -0.6 (-0.9, -0.2) P<0.01
Month 12 | -0.5 (-0.7, -0.3) | 0.4 (0.1, 0.8) | -1.0 (-1.3, -0.6) P<0.01
Randomized eyes that received study treatment

In a subgroup analysis of patients in this trial at month 12, younger patients (< 30 years) experienced a treatment effect of -1.1 D, as a combination of improvement in the CXL treatment arm (-0.5 D) and deterioration in the sham procedure/vehicle control arm (0.5 D). Older patients (≥ 30 years) in the CXL treatment arm experienced comparable improvement (-0.6 D) as younger patients (-0.5 D); however, in the sham procedure/vehicle control arm, older patients (-0.0 D) did not deteriorate as much as younger patients (0.5 D).

16 HOW SUPPLIED/STORAGE AND HANDLING

EPIOXA HD (riboflavin 5'-phosphate ophthalmic solution) 0.239%, and EPIOXA (riboflavin 5'-phosphate ophthalmic solution) 0.177%, are clear, yellow, ophthalmic solutions. EPIOXA HD and EPIOXA are co-packaged in an Epithelium-on Cross-linking Kit (NDC 25357-024-01) containing:

- One single-dose glass syringe containing 2 mL of EPIOXA HD 0.239% packaged in a foil pouch.
- One single-dose glass syringe containing 2 mL of EPIOXA 0.177% packaged in a foil pouch.

STORAGE AND HANDLING

Store kit refrigerated at 2°C to 8°C (36°F to 46°F). Do not freeze. Minimize exposure of the syringes to light once removed from their protective packaging.

For topical ophthalmic use. Single-dose only. Discard syringes after use.

EPIOXA HD and EPIOXA are for use only with the O2n System, the single-use O2n System Treatment Activation Card, and Boost Goggles.

17 PATIENT COUNSELING INFORMATION

- Advise patients that there may be discomfort in the treated eye and that sunglasses may help with light sensitivity.
- Instruct patients that they should contact their physician immediately if they experience severe pain in the treated eye or any sudden decrease in their vision.

EPIOXA HD, EPIOXA, the O2n System, and Boost Goggles are marketed by:

Avedro, a Glaukos company
30 North Avenue
Burlington, MA 01803
USA

Issued 10/2025
ML-000159 Rev 1

PRINCIPAL DISPLAY PANEL - Kit Carton

NDC 25357-024-01

Rx Only

Epithelium-on Cross-linking Kit

Epioxa™ HD
(riboflavin 5'- phosphate ophthalmic solution) 0.239%

co-packaged with

Epioxa™
(riboflavin 5'- phosphate ophthalmic solution) 0.177%

For Topical Ophthalmic Use Only

Use only with O2n™ System, O2n™ System Single-use Treatment
Activation Card, and Boost Goggles®.
Do NOT use if damaged. Single-dose. Discard unused portion.

GLAUKOS®